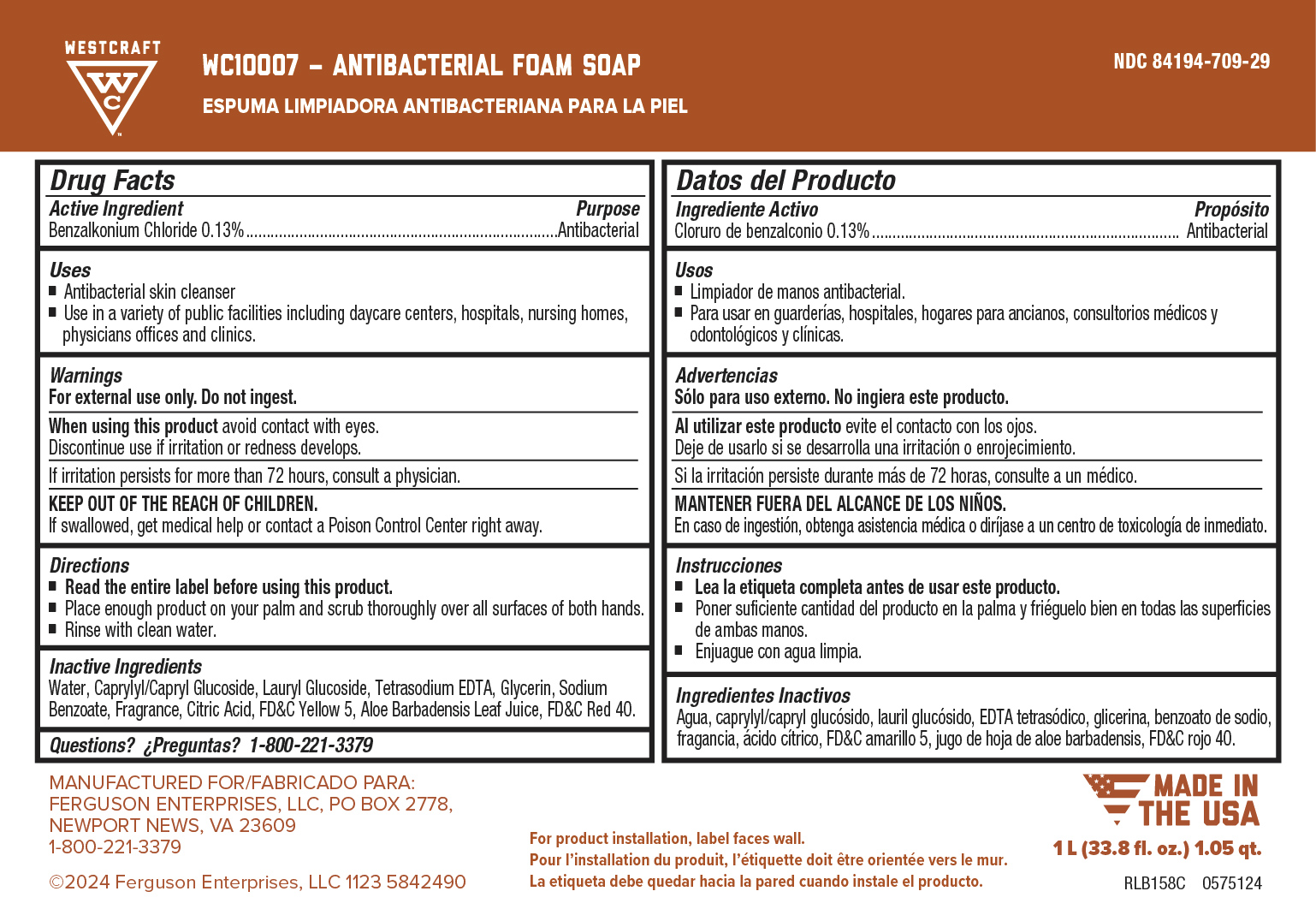 DRUG LABEL: Antibacterial FoamSoap
NDC: 84194-751 | Form: SOAP
Manufacturer: Ferguson Enterprises
Category: otc | Type: HUMAN OTC DRUG LABEL
Date: 20240624

ACTIVE INGREDIENTS: BENZALKONIUM CHLORIDE 1.3 mg/1 mL
INACTIVE INGREDIENTS: GLYCERIN; FD&C YELLOW NO. 5; ALOE VERA LEAF; FD&C RED NO. 40; METHYLCHLOROISOTHIAZOLINONE; ANHYDROUS CITRIC ACID; WATER; LAURAMINE OXIDE; METHYLISOTHIAZOLINONE; TETRASODIUM GLUTAMATE DIACETATE

WC10007 - Antibacterial Foam Soap

Active ingredient

Benzalkonium Chloride 0.13% w/w

Uses

Antibacterial skin cleanser

Effective in destroying harful bacteria to prevent antibacterial cleansing

Warnings

For external use only.

When using this product avoid contact with eyes. If contact occurs, rinse thoroughly with water.

Stop use and ask a doctor if irritation or rash occurs.

Keep out of the reach of children. If swallowed, get medical help or contact a Poison Control Center right away.

Directions

Read entire label before using this product.

Apply 5 milliliters (teaspoonful) or palmful to hands and forearms.

Scrub thoroughly for 20 seconds and rinse with clean water.

Inactive Ingredients

Aloe Barbadensis Leaf Juice, Citric Acid, FD&C Red 40, FD&C Yellow 5, Fragrance, Glycerin, Laurmine Oxide, Methylchloroisothiazolinone, Methylisothiazolinone, Tetrasodium Glutamate Diacetate, Water

Purpose

Antibacterial

Keep out of reach of children

Keep out of the reach of children